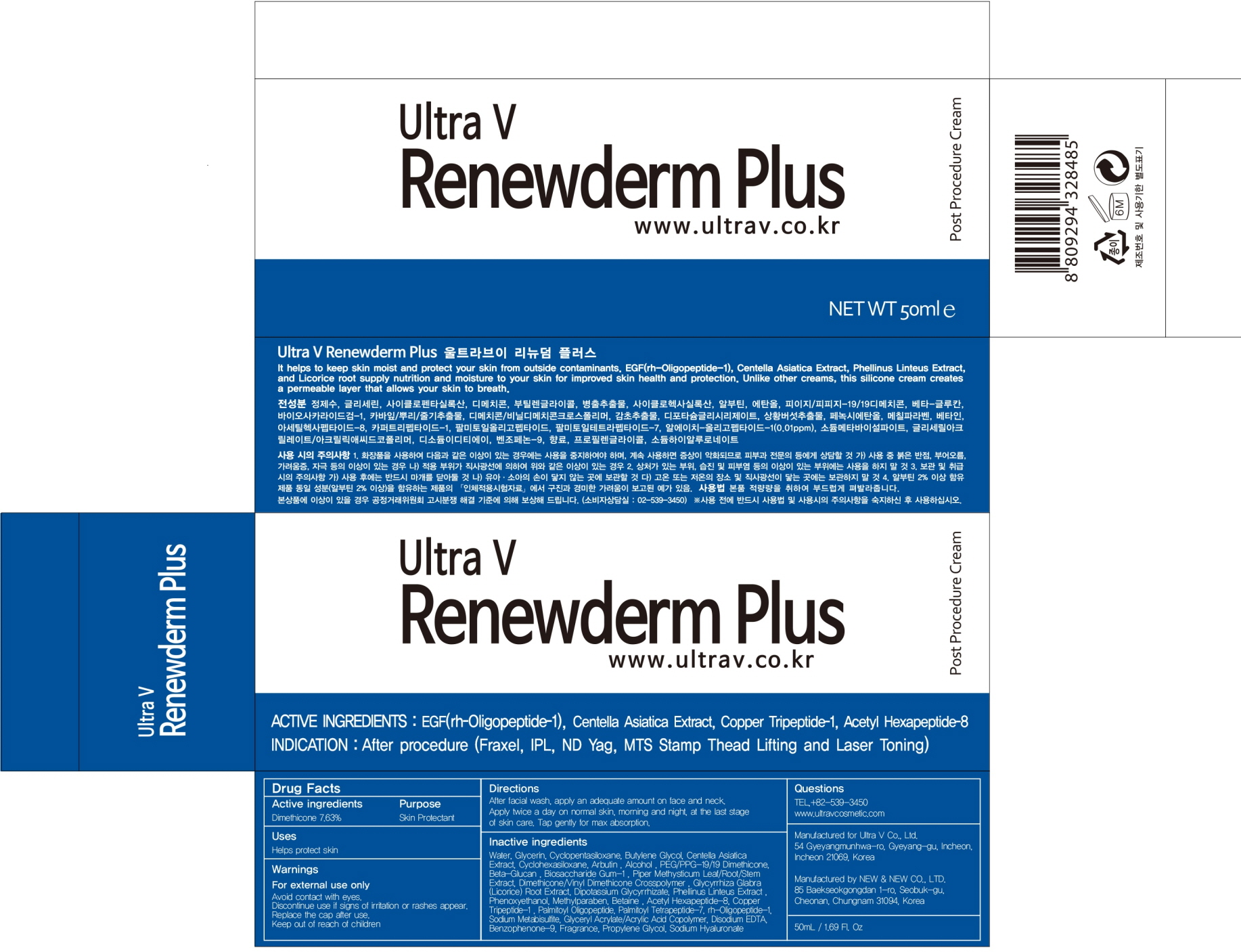 DRUG LABEL: Ultra V RENEWDERM PLUS
NDC: 71975-010 | Form: CREAM
Manufacturer: Ultra V Co., Ltd
Category: otc | Type: HUMAN OTC DRUG LABEL
Date: 20200401

ACTIVE INGREDIENTS: Dimethicone 3.81 g/50 mL
INACTIVE INGREDIENTS: Water; Glycerin

ACTIVE INGREDIENT

Active ingredients: Dimethicone 7.63%

INACTIVE INGREDIENT

Inactive ingredients: Water, Glycerin, Cyclopentasiloxane, Butylene Glycol, Centella Asiatica Extract, Cyclohexasiloxane, Arbutin , Alcohol , PEG/PPG-19/19 Dimethicone, Beta-Glucan , Biosaccharide Gum-1 , Piper Methysticum Leaf/Root/Stem Extract, Dimethicone/Vinyl Dimethicone Crosspolymer , Glycyrrhiza Glabra (Licorice) Root Extract, Dipotassium Glycyrrhizate, Phellinus Linteus Extract , Phenoxyethanol, Methylparaben, Betaine , Acetyl Hexapeptide-8, Copper Tripeptide-1 , Palmitoyl Oligopeptide, Palmitoyl Tetrapeptide-7, rh-Oligopeptide-1, Sodium Metabisulfite, Glyceryl Acrylate/Acrylic Acid Copolymer, Disodium EDTA, Benzophenone-9, Fragrance, Propylene Glycol, Sodium Hyaluronate

PURPOSE

Purpose: Skin Protectant

WARNINGS

Warnings: For external use only. Avoid contact with eyes. Discontinue use if signs of irritation or rashes appear. Replace the cap after use. Keep out of reach of children.

KEEP OUT OF REACH OF CHILDREN

Uses

Uses: Helps protect skin

Directions

Directions: After facial wash, apply an adequate amount on face and neck. Apply twice a day on normal skin, morning and night, at the last stage of skin care. Tap gently for max absorption.

QUESTIONS

TEL,+82-539-3450

www.ultravcosmetic.com